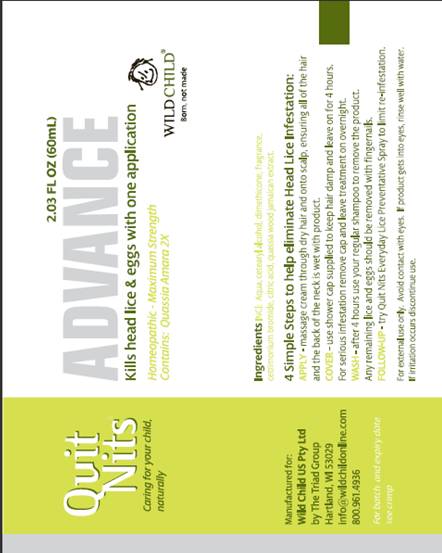 DRUG LABEL: Quit Nits Advance
NDC: 30807-2002 | Form: CREAM
Manufacturer: Wild Child W A Pty Ltd
Category: homeopathic | Type: HUMAN OTC DRUG LABEL
Date: 20091030

ACTIVE INGREDIENTS: quassia 2 [HP_X]/60 mL
INACTIVE INGREDIENTS: water; cetostearyl alcohol; dimethicone; cetrimonium bromide; citric acid monohydrate

DRUG FACTS

ACTIVE INGREDIENTS

Quassia amara 2X HPUS (Amargo 200mcg/g)

PURPOSE

Lice and egg treatment

USE

treats head lice, pubic (crab lice) and body lice

WARNINGS

For external use only.

DO NOT USE

- near eyes
- inside the nose, mouth or vagina
- on lice in eyebrows or eyelashes

See a doctor if lice are present in these areas.

WHEN USING THIS PRODUCT

- keep tightly closed and protect eyes with a washcloth or towel.
- if product gets into the eyes, flush with water right away.

STOP USE AND ASK A DOCTOR IF

- eye irritation occurs
- skin or scalp irritation continues or infection occurs

KEEP OUT OF REACH OF CHILDREN

If swallowed, get medical help or contact a Poison Control Center right away.

DIRECTIONS

Important: Read warnings and full directions. For more information read the enclosed Consumer Information Leaflet.
For adults and children 6 months and over.
APPLY

- apply the entire contents of one tube thoroughly to dry hair, starting from behind the ears to the back of the neck, working forward.
- to be effective, all lice and eggs must come in contact with product, ensure hair and scalp are saturated. For long or very thick hair two tubes may be required.

COVER

- use the shower cap supplied to keep hair damp, leave on for 4 hours before washing.
- for serious infestation remove shower cap after 4 hours and leave product on overnight.

WASH

- wash area thoroughly with warm water and regular shampoo. Towel hair dry and comb out tangles using a regular comb or brush.
- as an option remove any remaining lice or nits with the included nit comb or fingernails.
- if hair dries during combing dampen slightly with water.

OTHER INFORMATION

- keep carton for important product information
- protect from excessive heat

INACTIVE INGREDIENTS

aqua, cetearyl alcohol, dimethicone, fragrance, cetrimonium bromide, citric acid

QUESTIONS

800-961-4936 or

support@QuitNits.com

www.QuitNits.com

PACKAGING INFORMATION

Quit Nits®
Caring for your child, naturally
2.03 FL OZ (60mL)
ADVANCE
Kills head lice and eggs with one application
WILD CHILD®
Born, not made.
Ingredients Incl: Aqua, cetearyl alcohol, dimethicone, fragrance, cetrimonium bromide, citric acid, quassia wood jamaican extract.
4 simple steps to help eliminate Head Lice Infestation:
APPLY - Massage cream through dry hair and onto scalp, ensuring all of the hair and the back of the neck is wet with product.
COVER - Use shower cap supplied to keep hair damp and leave on for 4 hours. For serious infestation remove cap and leave treatment on overnight.
WASH - after 4 hours use your regular shampoo to remove the product. Any remaining lice and eggs should be removed with fingernails.
FOLLOW-UP try Quit Nits Every Day Lice Preventative Spray to limit re-infestation.
For external use only. Avoid contact with eyes. If product gets into eyes, rinse well with water. If irritation occurs, discontinue use.
Manufactured for:
Wild Child (US) Pty Ltd
by The Triad Group
Hartland, WI 53029
info@wildchildonline.com
800.961.4936
For batch and expiry date see crimp